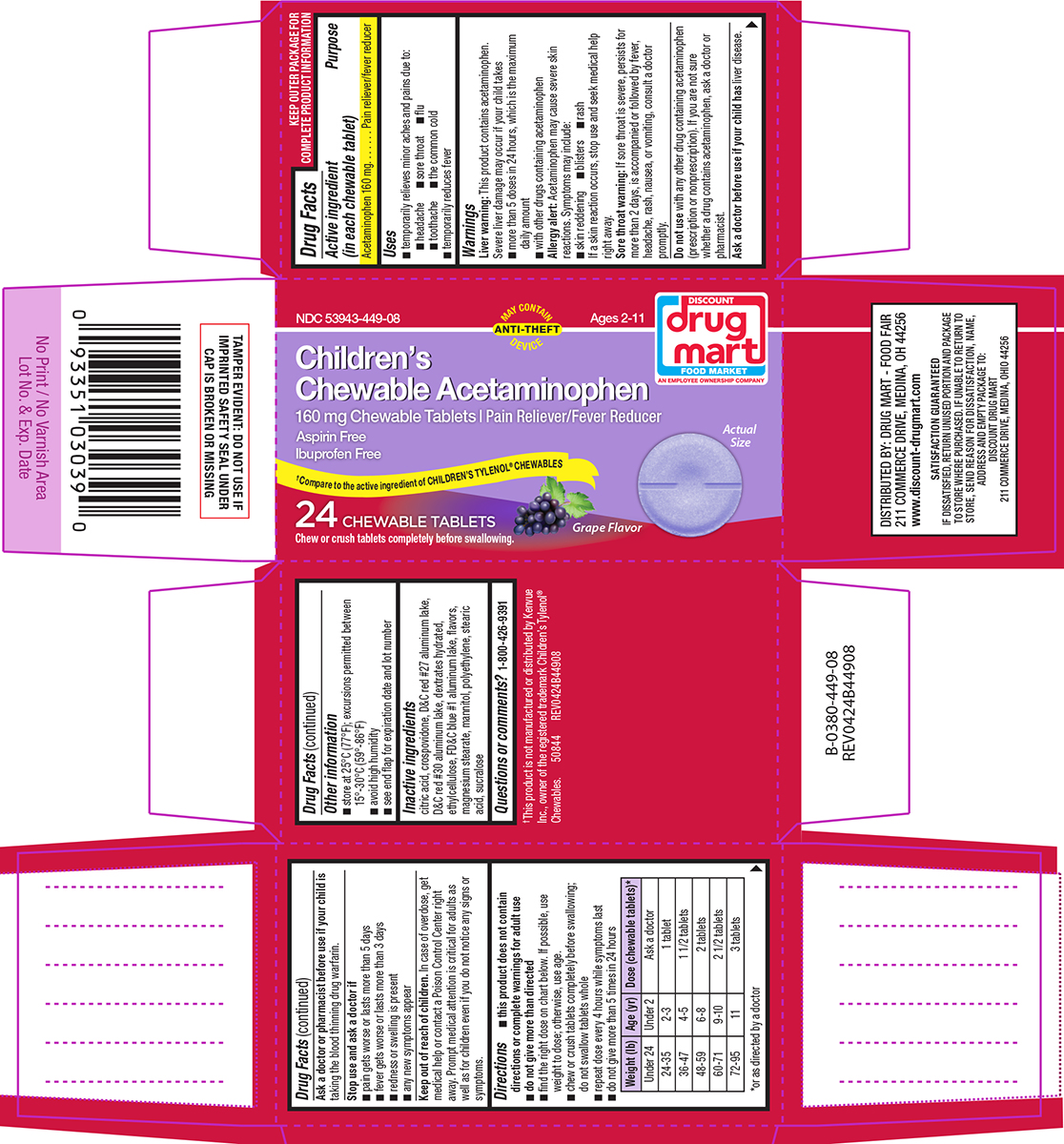 DRUG LABEL: Childrens Chewable Acetaminophen
NDC: 53943-449 | Form: TABLET, CHEWABLE
Manufacturer: Discount Drug Mart
Category: otc | Type: HUMAN OTC DRUG LABEL
Date: 20260226

ACTIVE INGREDIENTS: ACETAMINOPHEN 160 mg/1 1
INACTIVE INGREDIENTS: CITRIC ACID MONOHYDRATE; CROSPOVIDONE, UNSPECIFIED; D&C RED NO. 27 ALUMINUM LAKE; D&C RED NO. 30 ALUMINUM LAKE; DEXTROSE MONOHYDRATE; ETHYLCELLULOSE, UNSPECIFIED; FD&C BLUE NO. 1 ALUMINUM LAKE; MAGNESIUM STEARATE; MANNITOL; HIGH DENSITY POLYETHYLENE; STEARIC ACID; SUCRALOSE

Drug Mart 44-449

Active ingredient (in each chewable tablet)

Acetaminophen 160 mg

Purpose

Pain reliever/fever reducer

Uses

- temporarily relieves minor aches and pains due to:
  - headache
  - sore throat
  - flu
  - toothache
  - the common cold
- temporarily reduces fever

Warnings

Liver warning: This product contains acetaminophen. Severe liver damage may occur if your child takes

- more than 5 doses in 24 hours, which is the maximum daily amount
- with other drugs containing acetaminophen

Allergy alert: Acetaminophen may cause severe skin reactions. Symptoms may include:

- skin reddening
- blisters
- rash

If a skin reaction occurs, stop use and seek medical help right away.

Sore throat warning: If sore throat is severe, persists for more than 2 days, is accompanied or followed by fever, headache, rash, nausea, or vomiting, consult a doctor promptly.

Do not use

with any other drug containing acetaminophen (prescription or nonprescription). If you are not sure whether a drug contains acetaminophen, ask a doctor or pharmacist.

Ask a doctor before use if your child has

liver disease.

Ask a doctor or pharmacist before use if your child is

taking the blood thinning drug warfarin.

Stop use and ask a doctor if

- pain gets worse or lasts more than 5 days
- fever gets worse or lasts more than 3 days
- redness or swelling is present
- any new symptoms appear

Keep out of reach of children.

In case of overdose, get medical help or contact a Poison Control Center right away. Prompt medical attention is critical for adults as well as for children even if you do not notice any signs or symptoms.

Directions

- this product does not contain directions or complete warnings for adult use
- do not give more than directed
- find the right dose on chart below. If possible, use weight to dose; otherwise, use age.
- chew or crush tablets completely before swallowing; do not swallow tablets whole
- repeat dose every 4 hours while symptoms last
- do not give more than 5 times in 24 hours

Weight (lb) | Age (yr) | Dose (chewable tablets)*
Under 24 | Under 2 | Ask a doctor
24-35 | 2-3 | 1 tablet
36-47 | 4-5 | 1 1/2 tablets
48-59 | 6-8 | 2 tablets
60-71 | 9-10 | 2 1/2 tablets
72-95 | 11 | 3 tablets

*or as directed by a doctor

Other information

- store at 25°C (77°F); excursions permitted between 15°-30°C (59°-86°F)
- avoid high humidity
- see end flap for expiration date and lot number

Inactive ingredients

citric acid, crospovidone, D&C red #27 aluminum lake, D&C red #30 aluminum lake, dextrates hydrated, ethylcellulose, FD&C blue #1 aluminum lake, flavors, magnesium stearate, mannitol, polyethylene, stearic acid, sucralose

Questions or comments?

1-800-426-9391

Principal display panel

NDC 53943-449-08

MAY CONTAIN ANTI-THEFT DEVICE

Discount
Drug
Mart
FOOD MARKET
AN EMPLOYEE OWNERSHIP COMPANY

Ages 2-11

Children's
Chewable Acetaminophen
160 mg Chewable Tablets | Pain Reliever/Fever Reducer

Aspirin Free
Ibuprofen Free

†Compare to the active ingredient of CHILDREN'S TYLENOL® CHEWABLES

24 CHEWABLE TABLETS
Chew or crush tablets completely before swallowing.

Actual Size

Grape Flavor

TAMPER EVIDENT: DO NOT USE IF
IMPRINTED SAFETY SEAL UNDER
CAP IS BROKEN OR MISSING

†This product is not manufactured or distributed by Kenvue
Inc., owner of the registered trademark Children’s Tylenol®
Chewables. 50844 REV0424B44908

DISTRIBUTED BY: DRUG MART - FOOD FAIR
211 COMMERCE DRIVE, MEDINA, OH 44256
www.discount-drugmart.com

SATISFACTION GUARANTEED
IF DISSATISFIED, RETURN UNUSED PORTION AND PACKAGE
TO STORE WHERE PURCHASED. IF UNABLE TO RETURN TO
STORE, SEND REASON FOR DISSATISFACTION, NAME,
ADDRESS AND EMPTY PACKAGE TO:
DISCOUNT DRUG MART
211 COMMERCE DRIVE, MEDINA, OHIO 44256

Drug Mart 44-449